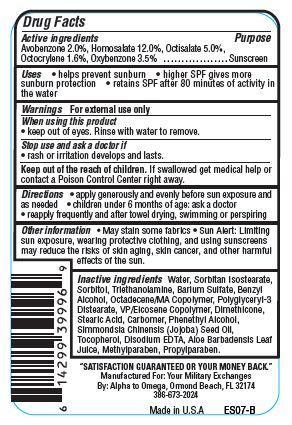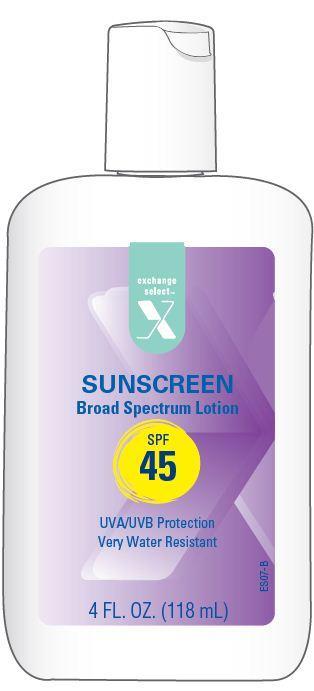 DRUG LABEL: Exchange Select Sunscreen
NDC: 55301-001 | Form: LOTION
Manufacturer: ARMY AND AIR FORCE EXCHANGE SERVICE
Category: otc | Type: HUMAN OTC DRUG LABEL
Date: 20121115

ACTIVE INGREDIENTS: AVOBENZONE 2 g/100 g; HOMOSALATE 12 g/100 g; OCTISALATE 5 g/100 g; OCTOCRYLENE 1.6 g/100 g; OXYBENZONE 3.5 g/100 g
INACTIVE INGREDIENTS: WATER; STEARIC ACID; SORBITAN ISOSTEARATE; SORBITOL; BARIUM SULFATE; POLYGLYCERYL-3 DIISOSTEARATE; PHENYLETHYL ALCOHOL; TROLAMINE; BENZYL ALCOHOL; DIMETHICONE; JOJOBA OIL; TOCOPHEROL; EDETATE DISODIUM; ALOE VERA LEAF; DIMETHICONE; METHYLPARABEN; PROPYLPARABEN

Drug Facts

Active ingredients

Avobenzone 2.0%
Homosalate 12.0%
Octisalate 5.0%
Octtocrylene 1.6%
Oxybenzone 3.5%

Purpose

Sunscreen

Uses

- helps prevent sunburn
- higher SPF gives more sunburn protection
- retains SPF after 80 minutes of activity in the water

Warnings

For external use only

When using this product

- keep out of eyes. Rinse with water to remove.

Stop use and ask a doctor if

- rash or irritation develops and lasts.

Keep Out of the reach of children.

If swallowed get medical help or contact a Poison Control Center right away.

Directions

- apply generously before sun exposure and as needed
- children under 6 months of age:ask a doctor
- reapply frequently and after towel drying, swimming or perspiring.

Other Information

- May stain some fabrics
- Sun Alert: Limiting sun exposure, wearing protective clothing, and using sunscreens may reduce the risks of skin aging, skin cance, and other harmful effects of the sun.

Inactive ingredients

Water, Sorbitan Isostearate, Sorbitol, Triethanolamine, Octadecene/MA Copolymer, Polyglyceryl-3 Distearate, VP/Eicosene Copolymer, Benzyl Alcohol, Barium Sulfate, Dimethicone, Stearic Acid, Carbomer, Phenethyl Alcohol, Simmondsia Chinensis (Jojoba) Seed Oil, Tocopherol, Disodium EDTA, Aloe Barbadensis Leaf Juice Powder, Methylparaben, Propylparaben.

Principal Display Panel

exchange
select
X
SUNSCREEN
Broad Spectrum Lotion
SPF
45
UVA/UVB Protection
Very Water Resistant
4 FL. OZ. (118 mL)